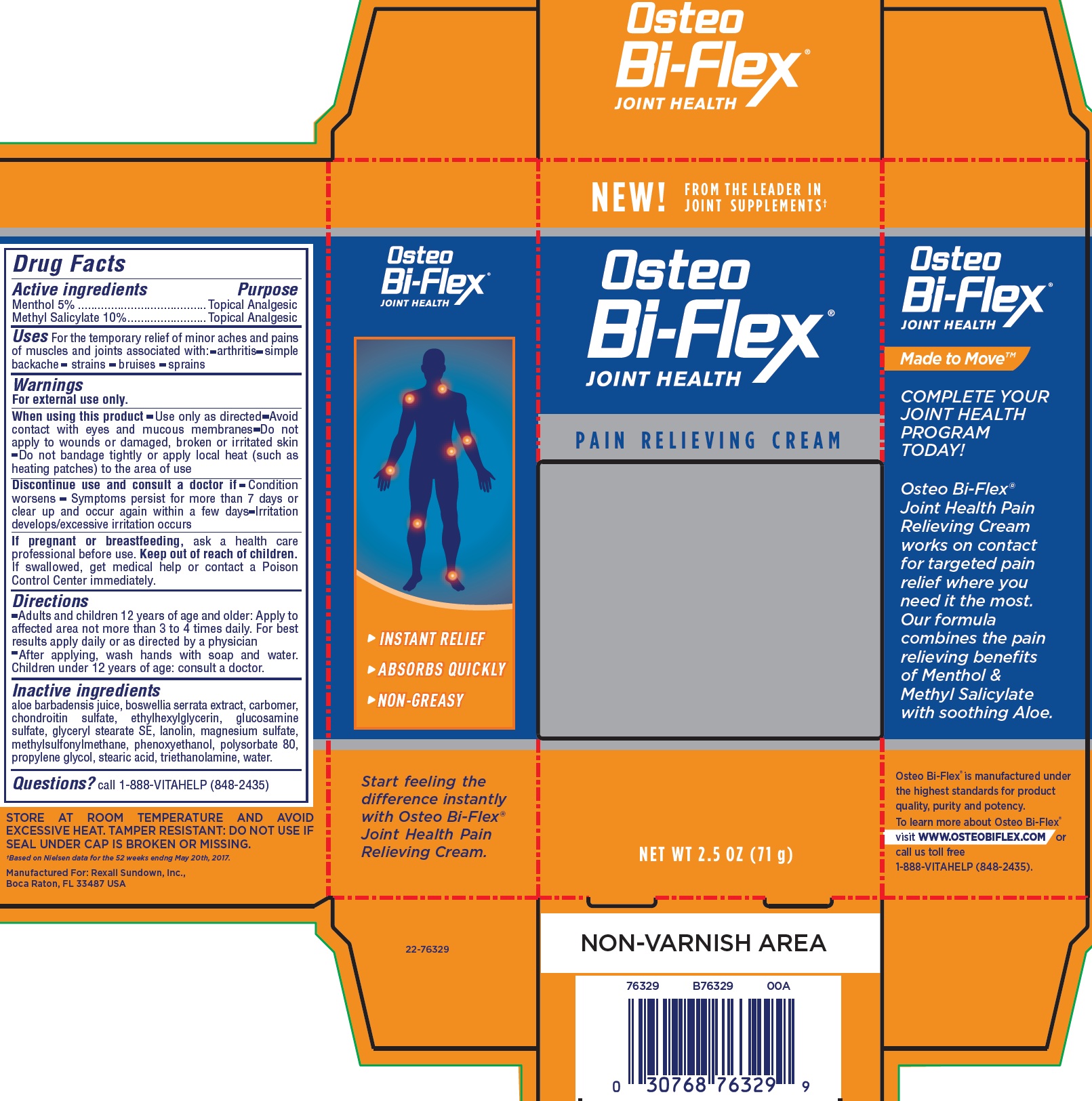 DRUG LABEL: Osteo Bi-Flex JOINT HEALTH PAIN RELIEVING
NDC: 59118-837 | Form: CREAM
Manufacturer: Rexall Sundown, LLC
Category: otc | Type: HUMAN OTC DRUG LABEL
Date: 20231110

ACTIVE INGREDIENTS: MENTHOL 50 mg/1 g; METHYL SALICYLATE 100 mg/1 g
INACTIVE INGREDIENTS: INDIAN FRANKINCENSE; CARBOXYPOLYMETHYLENE; ETHYLHEXYLGLYCERIN; GLUCOSAMINE SULFATE; GLYCERYL STEARATE SE; LANOLIN; MAGNESIUM SULFATE, UNSPECIFIED FORM; DIMETHYL SULFONE; PHENOXYETHANOL; POLYSORBATE 80; PROPYLENE GLYCOL; STEARIC ACID; TROLAMINE; WATER

Osteo Bi-Flex JOINT HEALTH PAIN RELIEVING CREAM

Active ingredients

Menthol 5%

Methyl Salicylate 10%

Purpose

Topical Analgesic

Uses

For the temporary relief of minor aches and pains of muscles and joints associated with: - arthritis - simple backache - strains - bruises - sprains

Warnings

For external use only.

When using this product

- Use only as directed
- Avoid contact with eyes and mucous membranes
- Do not apply to wounds or damaged, broken or irritated skin
- Do not bandage tightly or apply local heat (such as heating patches) to the area of use

Discontinue use and consult a doctor if

- Condition worsens
- Symptoms persist for more than 7 days or clear up and occur again within a few days
- Irritation develops/excessive irritation occurs

If pregnant or breastfeeding

ask a health care professional before use.

Keep out of reach of children.

If swallowed, get medical help or contact a Poison Control Center immediately.

Directions

- Adults and children 12 years of age and older: Apply to affected area not more than 3 to 4 times daily. For best results apply daily or as directed by a physician
- After applying, wash hands with soap and water. Children under 12 years of age: consult a doctor.

Inactive ingredients

aloe barbadensis juice, boswellia serrata extract, carbomer, chondroitin sulfate, ethylhexylglycerin, glucosamine sulfate, glyceryl stearate SE, lanolin, magnesium sulfate, methylsulfonylmethane, phenoxyethanol, polysorbate 80, propylene glycol, stearic acid, triethanolamine, water.

Questions?

call 1-888-VITAHELP (848-2435)